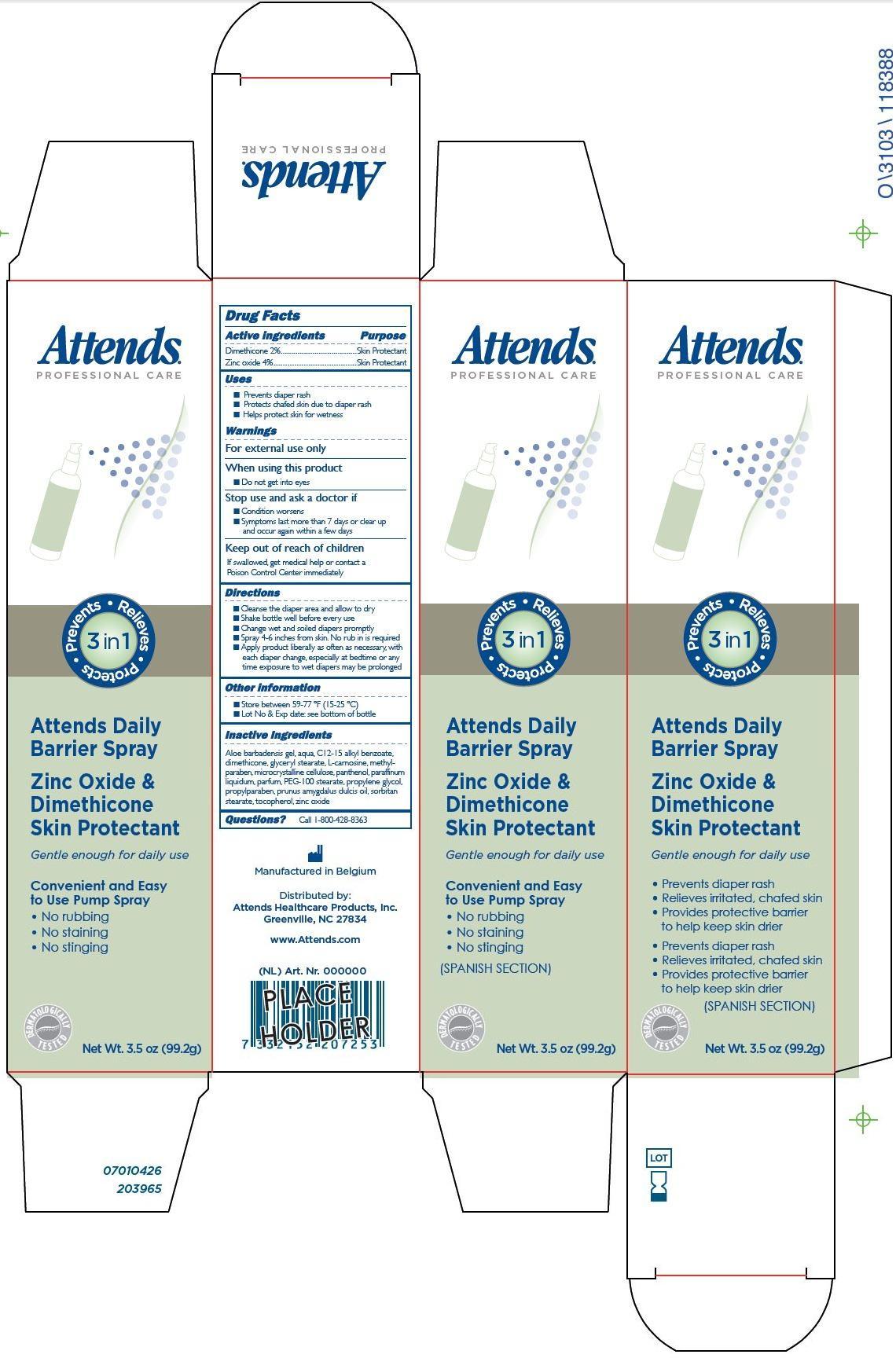 DRUG LABEL: Attends Daily Barrier
NDC: 62450-001 | Form: SPRAY
Manufacturer: Purna Pharmaceuticals NV
Category: otc | Type: HUMAN OTC DRUG LABEL
Date: 20140306

ACTIVE INGREDIENTS: ZINC OXIDE 4 g/99 g; DIMETHICONE 2 g/99 g
INACTIVE INGREDIENTS: ALOE VERA LEAF; WATER; C12-15 ALKYL BENZOATE; GLYCERYL MONOSTEARATE; CARNOSINE; METHYLPARABEN; CELLULOSE, MICROCRYSTALLINE; PANTHENOL; MINERAL OIL; PEG-100 STEARATE; PROPYLENE GLYCOL; PROPYLPARABEN; ALMOND OIL; SORBITAN MONOSTEARATE; TOCOPHEROL

Active Ingredient Purpose

Dimethicone 2% ............................... Skin Protectant

Zinc Oxide 4% .................................. Skin Protectant

PURPOSE

Attends Professional Care

Prevents. Treats. Protects. 3in1

Attends Daily Barrier S[ray

Zinc Oxide & Dimethicone Skin Protectant

Gentle enough for daily use

Convenient and easy to use Pump Spray

- No rubbing
- No staining
- No stinging

(Spanish Panel)

- Prevents diaper rash
- Treats irritated, chafed skin
- Provides protective barrier to help keep skin drier

(Spanish Section

Dermatologically Tested

Net Wt. 3.5 oz (99.2 g)

Keep out of reach of children.

If swallowed, get medical help or contact a Poison Control Center immediately.

Uses

- Prevents diaper rash
- Protects chafed skin due to diaper rash
- Helps protect skin for wetness

Warnings

For external use only

When using this product

- Do not get into eyes

Stop use and ask a doctor if

- Condition worsens
- Symptoms last more than 7 days or clear up and occur again within a few days

Directions

- Cleanse the diaper area and allow to dry
- Shake bottle well before every use
- Change wet and soiled diapers promptly
- Spray 4-6 inches from skin. No rub in is required
- Apply product liberally as often as necessary, with each dipaer change, especially at bedtime or any time exposure to wet diapers may be prolonged

Other Information

- Store between 59-77oF (15-25oC)
- Lot No & Exp date: see bottom of bottle

Questions? Call 1-800-428-8363

Manufactured in Belgium

Distributed by:

Attends Healthcare Products, Inc.

Greenville, NC 27834

www.Attends.com

Inactive Ingredients

aloe barbadensis gel, aqua, C12-15 alkyl benzoate, dimethicone, glyceryl stearate, L-Carnoside, methylparaben, microcrystalline cellulose, panthenol, paraffinum liquidum, parfum, PEG-100 stearate, propylene glycol, propylparaben, prunus amygdalus dulcis oil, sorbitan stearate, tocopherol, zinc oxide.